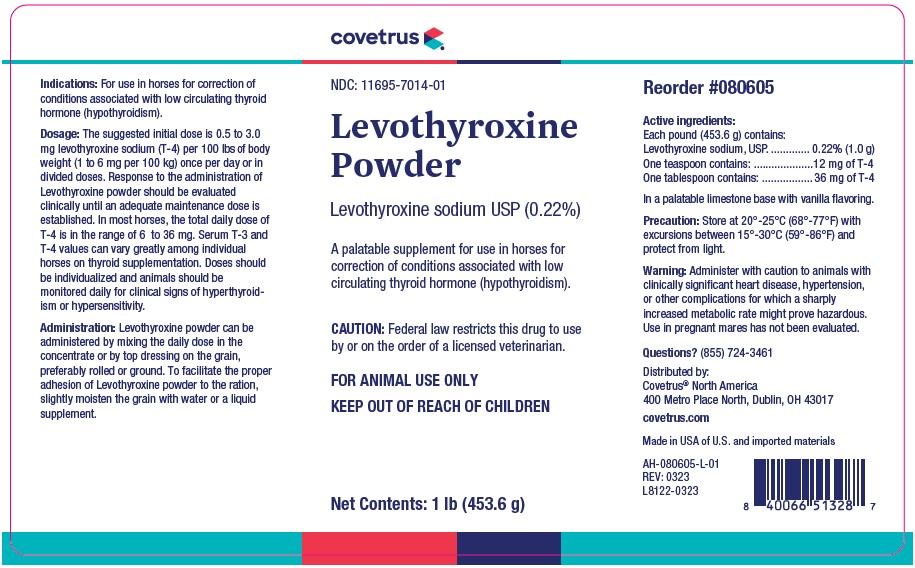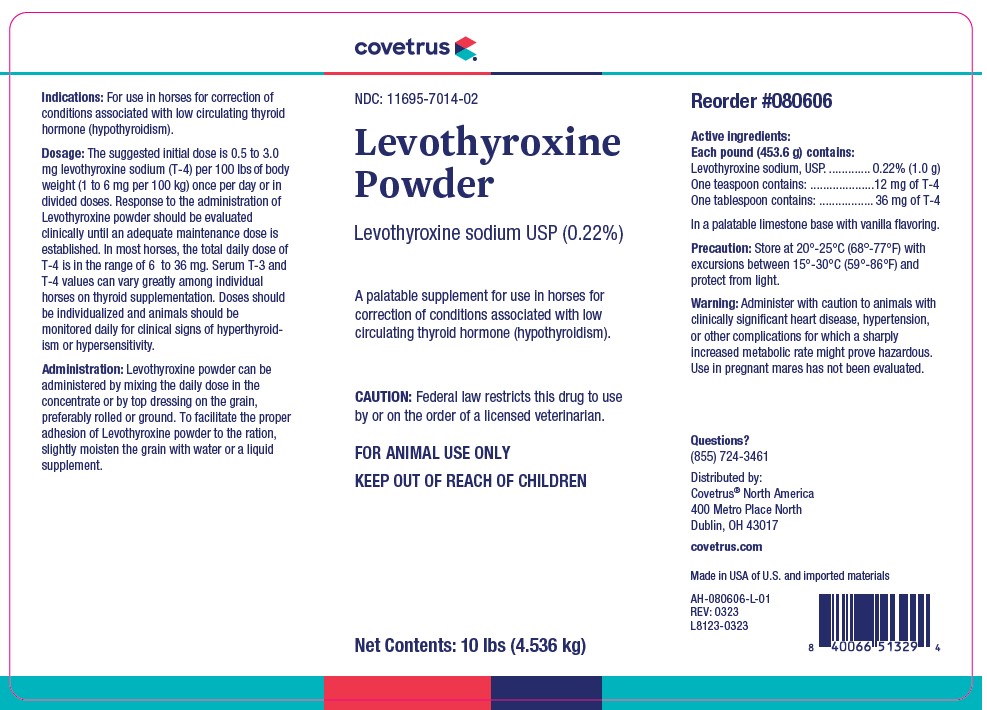 DRUG LABEL: Levothyroxine Powder
NDC: 11695-7014 | Form: POWDER
Manufacturer: Covetrus North America
Category: animal | Type: PRESCRIPTION ANIMAL DRUG LABEL
Date: 20251205

ACTIVE INGREDIENTS: LEVOTHYROXINE SODIUM 1 g/453.6 g

Levothyroxine Powder

INDICATIONS AND USAGE

Indications: For use in horses for correction of conditions associated with low circulating thyroid hormone (hypothyroidism).

DOSAGE AND ADMINISTRATION

Dosage: The suggested initial dose is 0.5 to 3.0mg levothyroxine sodium (T-4) per 100 lbs of body weight (1 to 6 mg per 100 kg) once per day or in divided doses. Response to the administration of Levothyroxine powder should be evaluated clinically until an adequate maintenance dose is established. In most horses, the total daily dose of T-4 is in the range of 6 to 36 mg. Serum T-3 and T-4 values can vary greatly among individual horses on thyroid supplementation. Doses should be individualized and animals should be monitored daily for clinical signs of hyperthyroidism or hypersensitivity.

Administration: Levothyroxine powder can be administered by mixing the daily dose in the concentrate or by top dressing on the grain, preferably rolled or ground. To facilitate the proper adhesion of Levothyroxine powder to the ration, slightly moisten the grain with water or a liquid supplement.

COMPONENTS

Active ingredients:
Each pound (453.6 g) contains:
Levothyroxine sodium, USP. ............. 0.22% (1.0 g)
One teaspoon contains: ....................12 mg of T-4
One tablespoon contains: ................. 36 mg of T-4
In a palatable limestone base with vanilla flavoring.

STORAGE AND HANDLING

Precaution: Store at 20°-25°C (68°-77°F) with excursions between 15°-30°C (59°-86°F) and protect from light.

WARNINGS AND PRECAUTIONS

Warning: Administer with caution to animals with clinically significant heart disease, hypertension, or other complications for which a sharply increased metabolic rate might prove hazardous. Use in pregnant mares has not been evaluated.

Questions?
(855) 724-3461
Distributed by:
Covetrus® North America
400 Metro Place North
Dublin, OH 43017
covetrus.com
Made in USA of U.S. and imported materials

PRINCIPAL DISPLAY PANEL 1 Pound Jar

NDC: 11695-7014-01
Levothyroxine Powder
Levothyroxine sodium USP (0.22%)
A palatable supplement for use in horses for
correction of conditions associated with low
circulating thyroid hormone (hypothyroidism).
CAUTION: Federal law restricts this drug to use by or on the order of a licensed veterinarian
FOR ANIMAL USE ONLY
KEEP OUT OF REACH OF CHILDREN
Net Contents: 1 lb (453.6 g)

PRINCIPAL DISPLAY PANEL 10 Pound Pail

NDC: 11695-7014-02

Levothyroxine Powder
Levothyroxine sodium USP (0.22%)

A palatable supplement for use in horses for
correction of conditions associated with low
circulating thyroid hormone (hypothyroidism).

CAUTION: Federal law restricts this drug to use by or on the order of a licensed veterinarian

FOR ANIMAL USE ONLY
KEEP OUT OF REACH OF CHILDREN

Net Contents: 10 lbs (4.536 kg)